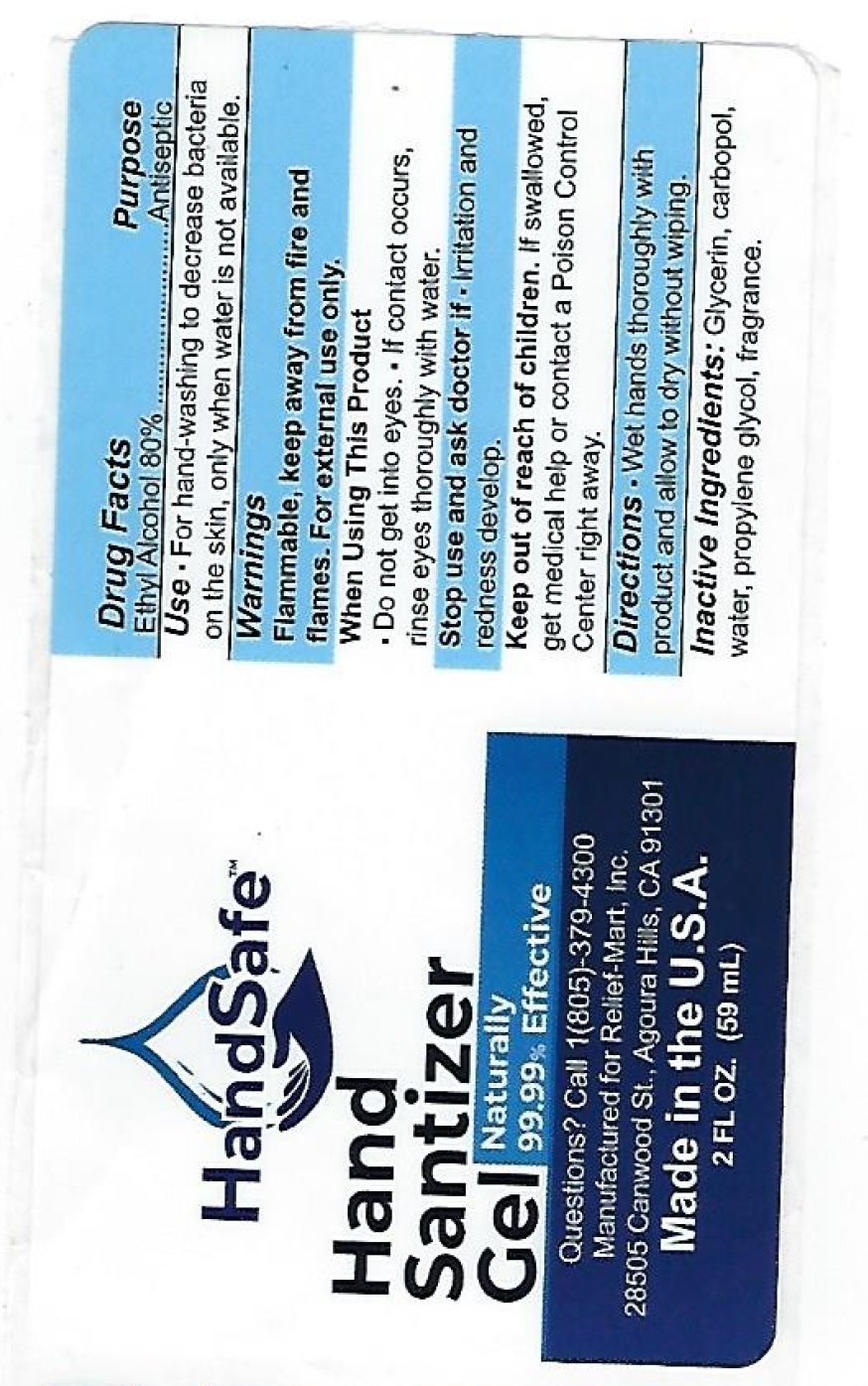 DRUG LABEL: Alcohol
NDC: 67285-104 | Form: GEL
Manufacturer: Relief-Mart, Inc
Category: otc | Type: HUMAN OTC DRUG LABEL
Date: 20220113

ACTIVE INGREDIENTS: ALCOHOL 80 mL/100 mL
INACTIVE INGREDIENTS: WATER 9.4 g/100 mL; CARBOMER HOMOPOLYMER, UNSPECIFIED TYPE 0.4 g/100 mL; ALOE VERA LEAF 0.2 g/100 mL; PROPYLENE GLYCOL 5 g/100 mL; GLYCERIN 5 g/100 mL; AMINOMETHYLPROPANOL 0.25 g/100 mL

Hand Sanitizer

Use

Use - For hand-washing to decrease bacteria on the skin, only when water is not available.

Purpose

Antiseptic

Stop Use

irritation and redness develop

Warning Section

Flammable, keep away from fire and flames. For external use only.

Directions

Wet hands thoroughly with product and allow to dry without wiping.

Keep out of reach of children

If swallowed, get medical help or contact a poison control center right away.

Inactive Ingredients

Glycerin, carbopol, water, propylene glycol, fragrance